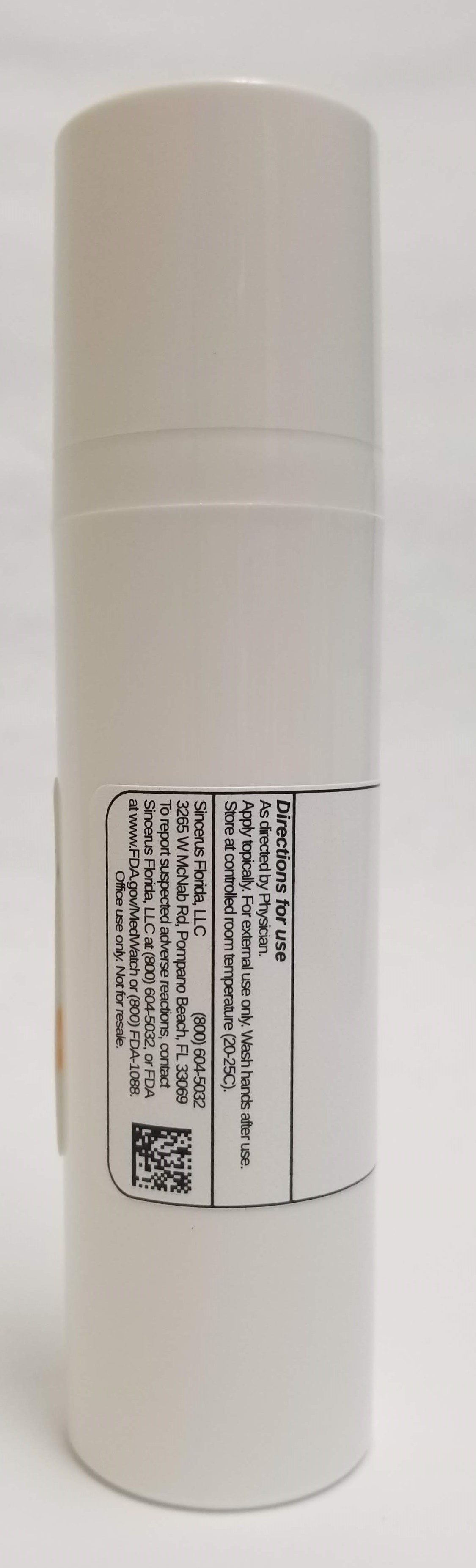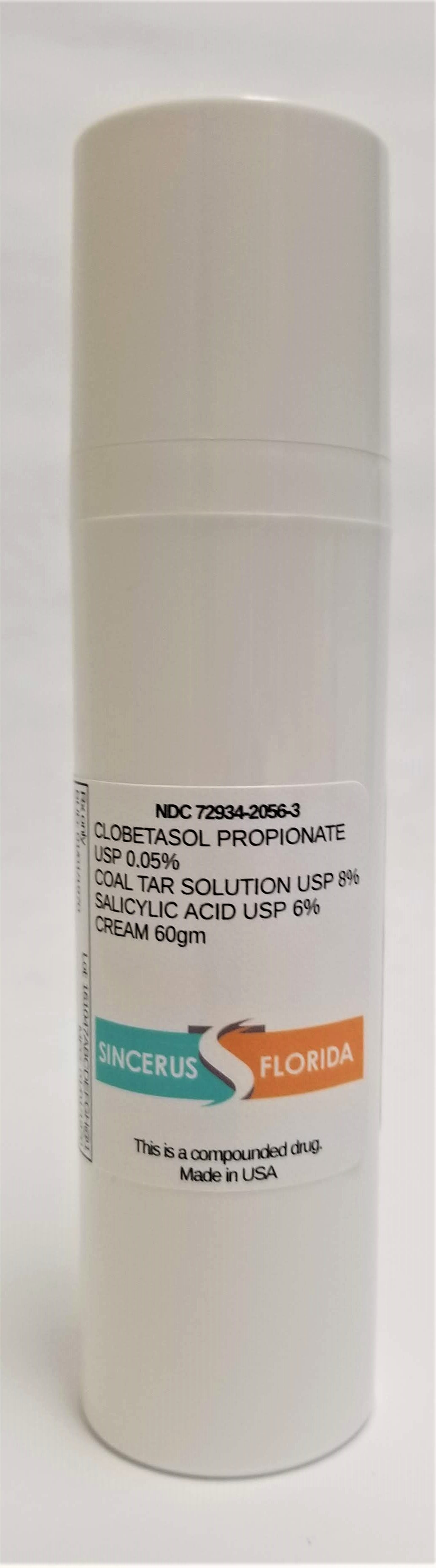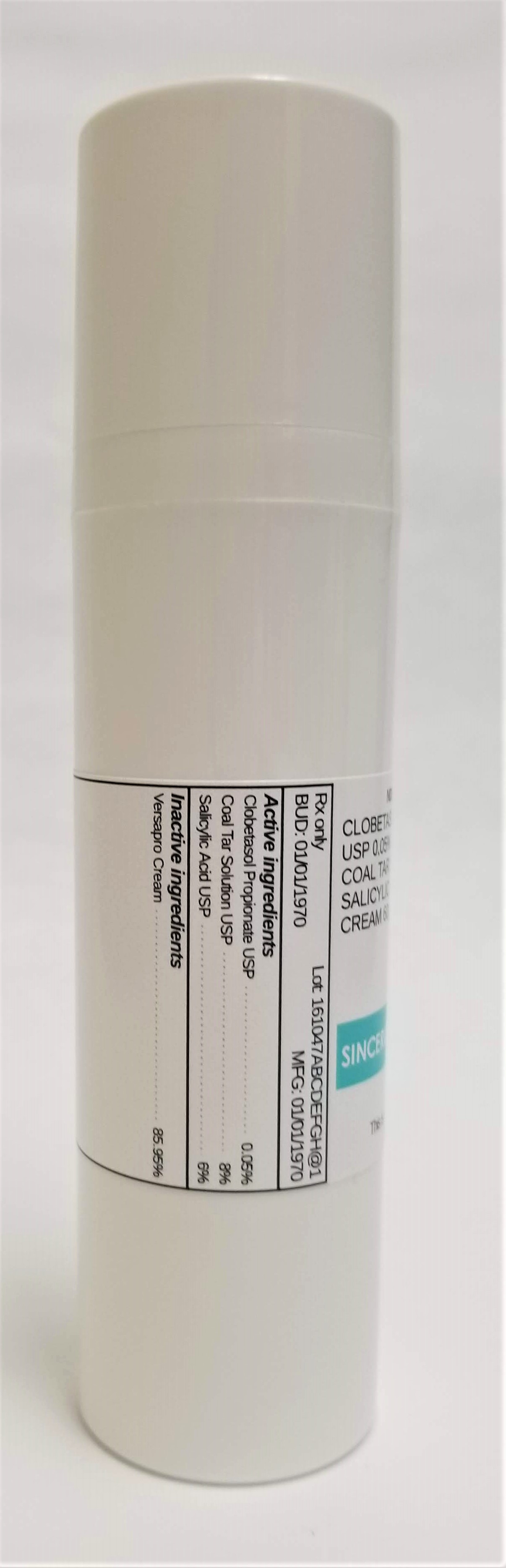 DRUG LABEL: CLOBETASOL PROPIONATE 0.05% / COAL TAR  8% / SALICYLIC ACID 6%
NDC: 72934-2056 | Form: CREAM
Manufacturer: Sincerus Florida, LLC
Category: prescription | Type: HUMAN PRESCRIPTION DRUG LABEL
Date: 20190514

ACTIVE INGREDIENTS: COAL TAR 8 g/100 g; SALICYLIC ACID 6 g/100 g; CLOBETASOL PROPIONATE 0.05 g/100 g

CLOBETASOL PROPIONATE 0.05% / COAL TAR SOLUTION 8% / SALICYLIC ACID 6%